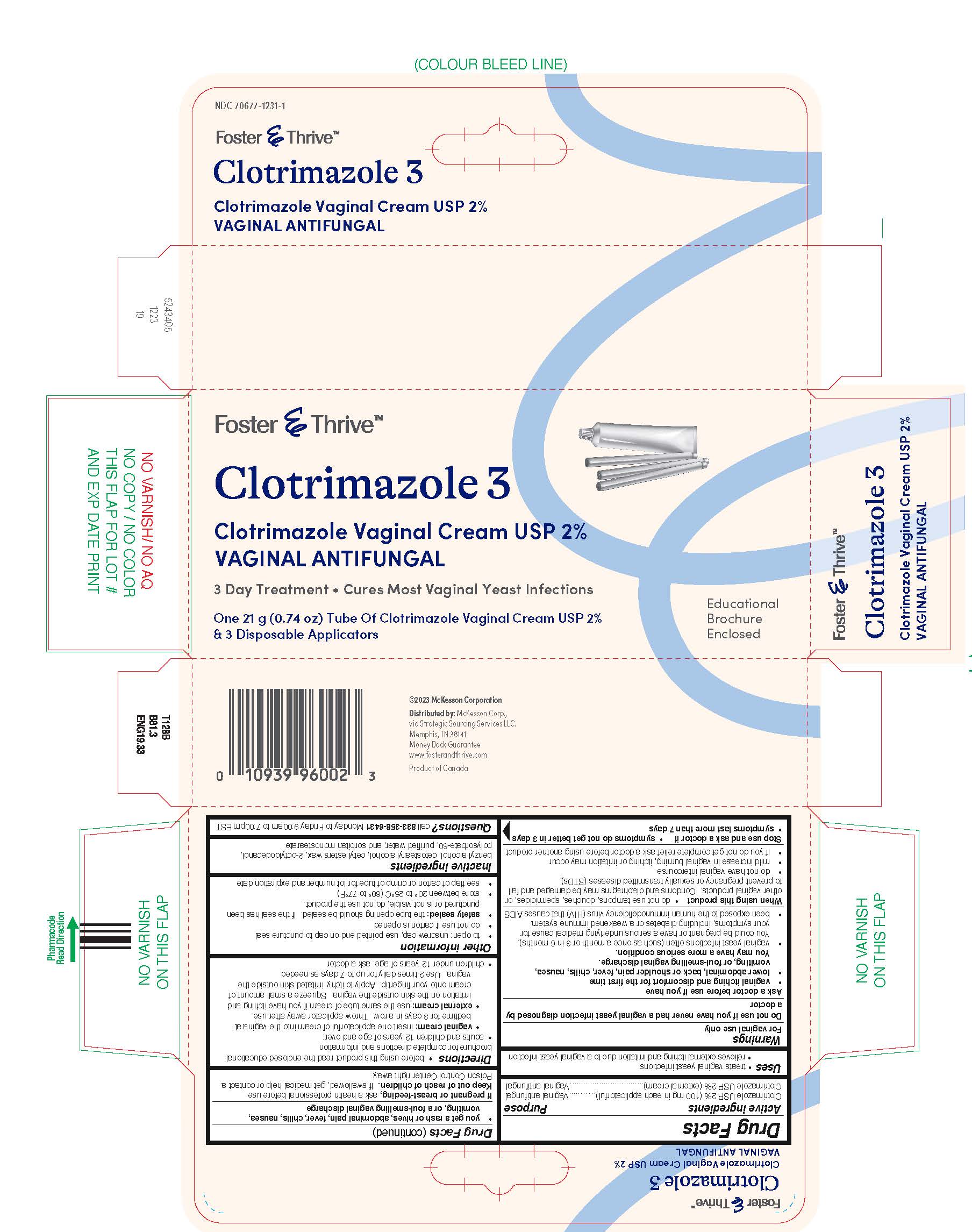 DRUG LABEL: Clotrimazole
NDC: 70677-1231 | Form: CREAM
Manufacturer: Foster and Thrive (Mckesson /STRATEGIC SOURCING SERVICES LLC)
Category: otc | Type: HUMAN OTC DRUG LABEL
Date: 20250730

ACTIVE INGREDIENTS: CLOTRIMAZOLE 2 g/100 g
INACTIVE INGREDIENTS: BENZYL ALCOHOL; CETOSTEARYL ALCOHOL; CETYL ESTERS WAX; OCTYLDODECANOL; POLYSORBATE 60; WATER; SORBITAN MONOSTEARATE

Clotrimazole

Drug Facts

ACTIVE INGREDIENT

Active ingredients | Purpose
Clotrimazole USP 2% (100 mg in each applicatorful) | Vaginal antifungal
Clotrimazole USP 2% (external cream) | Vaginal antifungal

Uses

- treats vaginal yeast infections
- relieves external itching and irritation due to a vaginal yeast infection

Warnings

For vaginal use only

Do not use if you have never had a vaginal yeast infection diagnosed by a doctor

Ask a doctor before use if you have

- vaginal itching and discomfort for the first time
- lower abdominal, back or shoulder pain, fever, chills, nausea, vomiting, or foul-smelling vaginal discharge.
  You may have a more serious condition.
- vaginal yeast infections often (such as once a month or 3 in 6 months). You could be pregnant or have a serious underlying medical cause for your symptoms, including diabetes or a weakened immune system.
- been exposed to the human immunodeficiency virus (HIV) that causes AIDS

When using this product

- do not use tampons, douches, spermicides, or other vaginal products. Condoms and diaphragms may be damaged and fail to prevent pregnancy or sexually transmitted diseases (STDs).
- do not have vaginal intercourse
- mild increase in vaginal burning, itching or irritation may occur
- if you do not get complete relief ask a doctor before using another product

Stop use and ask a doctor if

- symptoms do not get better in 3 days
- symptoms last more than 7 days
- you get a rash or hives, abdominal pain, fever, chills, nausea, vomiting, or a foul-smelling vaginal discharge

PREGNANCY OR BREAST FEEDING

If pregnant or breast-feeding,ask a health professional before use.

Keep out of reach of children.If swallowed, get medical help or contact a Poison Control Center right away.

Directions

- before using this product read the enclosed educational brochure for complete directions and information
- adults and children 12 years of age and over:
  - vaginal cream:insert one applicatorful of cream into the vagina at bedtime for 3 days in a row. Throw applicator away after use.
  - external cream:use the same tube of cream if you have itching and irritation on the skin outside the vagina. Squeeze a small amount of cream onto your fingertip. Apply to itchy, irritated skin outside the vagina. Use 2 times daily for up to 7 days as needed.
- children under 12 years of age: ask a doctor

Other information

- to open: unscrew cap, use pointed end on cap to puncture seal
- do not use if carton is opened
- safety sealed:the tube opening should be sealed. If the seal has been punctured or is not visible, do not use the product.
- store between 20° to 25°C (68° to 77°F)
- see flap of carton or crimp of tube for lot number and expiration date

Inactive ingredients

benzyl alcohol, cetostearyl alcohol, cetyl esters wax, 2-octyldodecanol, polysorbate-60, purified water, and sorbitan monostearate

Questions?

call 833-358-6431Monday to Friday 9:00am to 7:00pm EST

Distributed by:McKesson Corp.,
via Strategic Sourcing Services LLC.
Memphis, TN 38141

PRINCIPAL DISPLAY PANEL - 21 g Tube Carton

Foster & Thrive™

Clotrimazole 3

Clotrimazole Vaginal Cream USP 2%
VAGINAL ANTIFUNGAL

3 Day Treatment ∙ Cures Most Vaginal Yeast Infections

One 21 g (0.74 oz) Tube Of Clotrimazole Vaginal Cream USP 2%
& 3 Disposable Applicators

Educational
Brochure
Enclosed